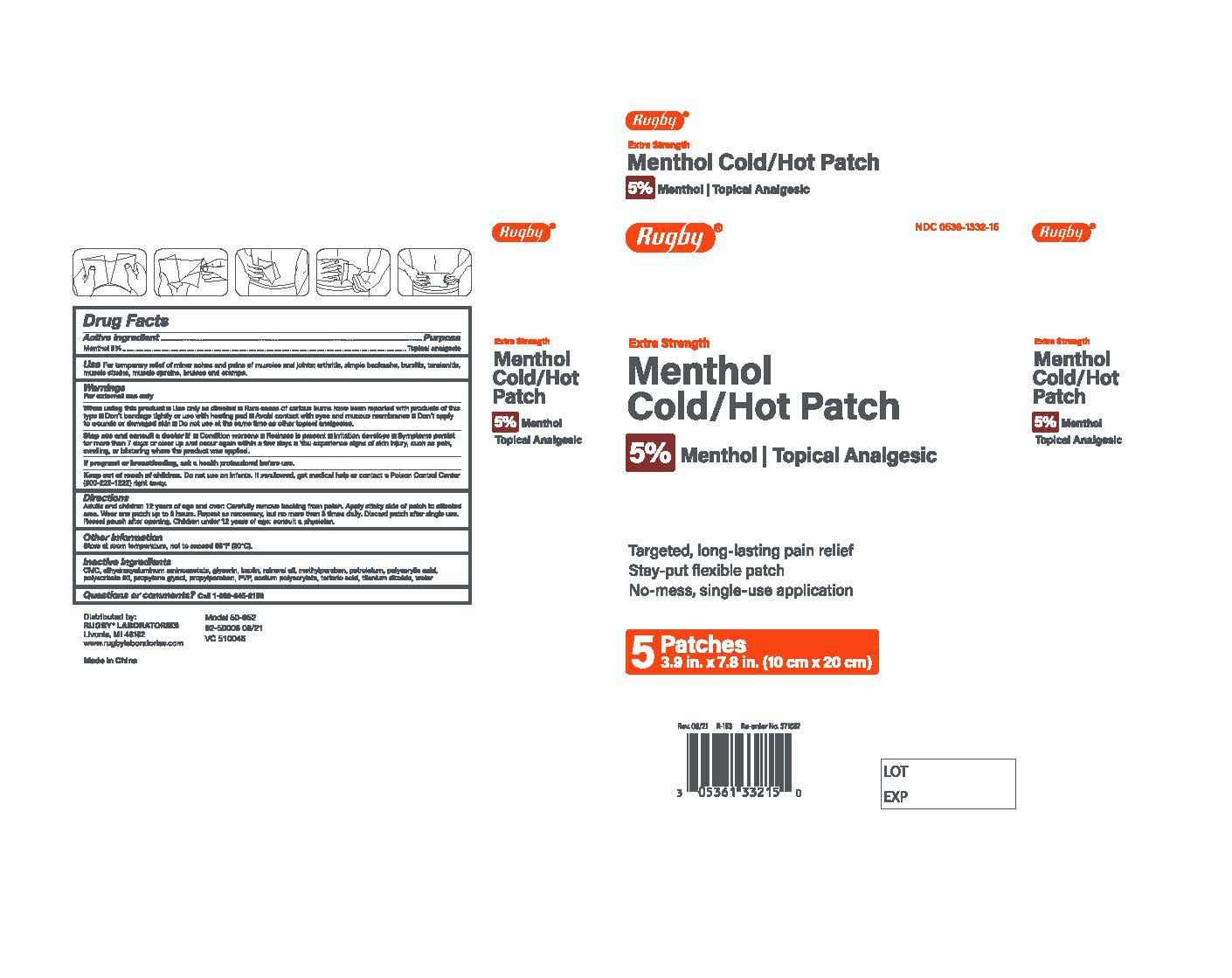 DRUG LABEL: Rugby Menthol Hot Cold Patch
NDC: 0536-1332 | Form: PATCH
Manufacturer: RUGBY LABORATORIES
Category: otc | Type: HUMAN OTC DRUG LABEL
Date: 20251208

ACTIVE INGREDIENTS: MENTHOL, UNSPECIFIED FORM 5 g/100 g
INACTIVE INGREDIENTS: DIHYDROXYALUMINUM AMINOACETATE; MINERAL OIL; GLYCERIN; KAOLIN; METHYLPARABEN; POLYACRYLIC ACID (8000 MW); POLYSORBATE 80; PROPYLENE GLYCOL; PETROLATUM; POVIDONE, UNSPECIFIED; PROPYLPARABEN; TARTARIC ACID; TITANIUM DIOXIDE; WATER; CARBOXYMETHYLCELLULOSE; SODIUM POLYACRYLATE (8000 MW)

Rugby 5% Menthol Hot/Cold Patch

Active Ingredients

Menthol 5% . . . . . . . . . . . . . . . . . . . . . . . . . . . . . . Topical Analgesic

Purpose

Topical analgesic

Warnings

For external use only

When using this product

■ use only as directed

■ Rare cases of serious burns have been reported with products of this type

■ don't bandage tightly or use with a heating pad

■ Avoid contact with the eyes and mucous membranes

■Don't apply to wounds or damaged skin

■ do not use at the same time as other topical analgesics

Stop use and consult a doctor

■ condition worsens

■ redness is present

■ irritation develops

■ symptoms persist for more than 7 days or clear up and occur again within a few days

■ you experience signs of skin injury, such as pain, swelling or blistering where the product was applied.

PREGNANCY OR BREAST FEEDING

If pregnant or breastfeeding, ask a health professional before use.

Keep out of reach of children

Do not use on infants. If swallowed, get medical help or contact a Poison Control Center (800-222-1222) right away.

Directions

Directions Adults and children 12 years of age and over:

- carefully remove backing from patch
- apply sticky side of patch to affected area
- wear one patch up to 8 hours
- repeat as necessary, but no more than 3 times daily
- discard patch after single use
- reseal pouch after opening.
- Children under 12 years of age: consult a physician.

Other safety information

Store at room temperature, not to exceed 86F (30C)

Inactive Ingredients

CMC, dihydroxyaluminum aminoacetate, Glycerin, Kaolin, Mineral Oil, Methylparaben, Petrolatum, Polyacrylic Acid, Polysorbate 80, Propylene Glycol, Propylparaben, PVP, Sodium Polyacrylate, Tartaric Acid, Titanium Dioxide, Water

Questions

Call 1-800-645-2158

INDICATIONS AND USAGE

Targeted, long-lasting pain relief